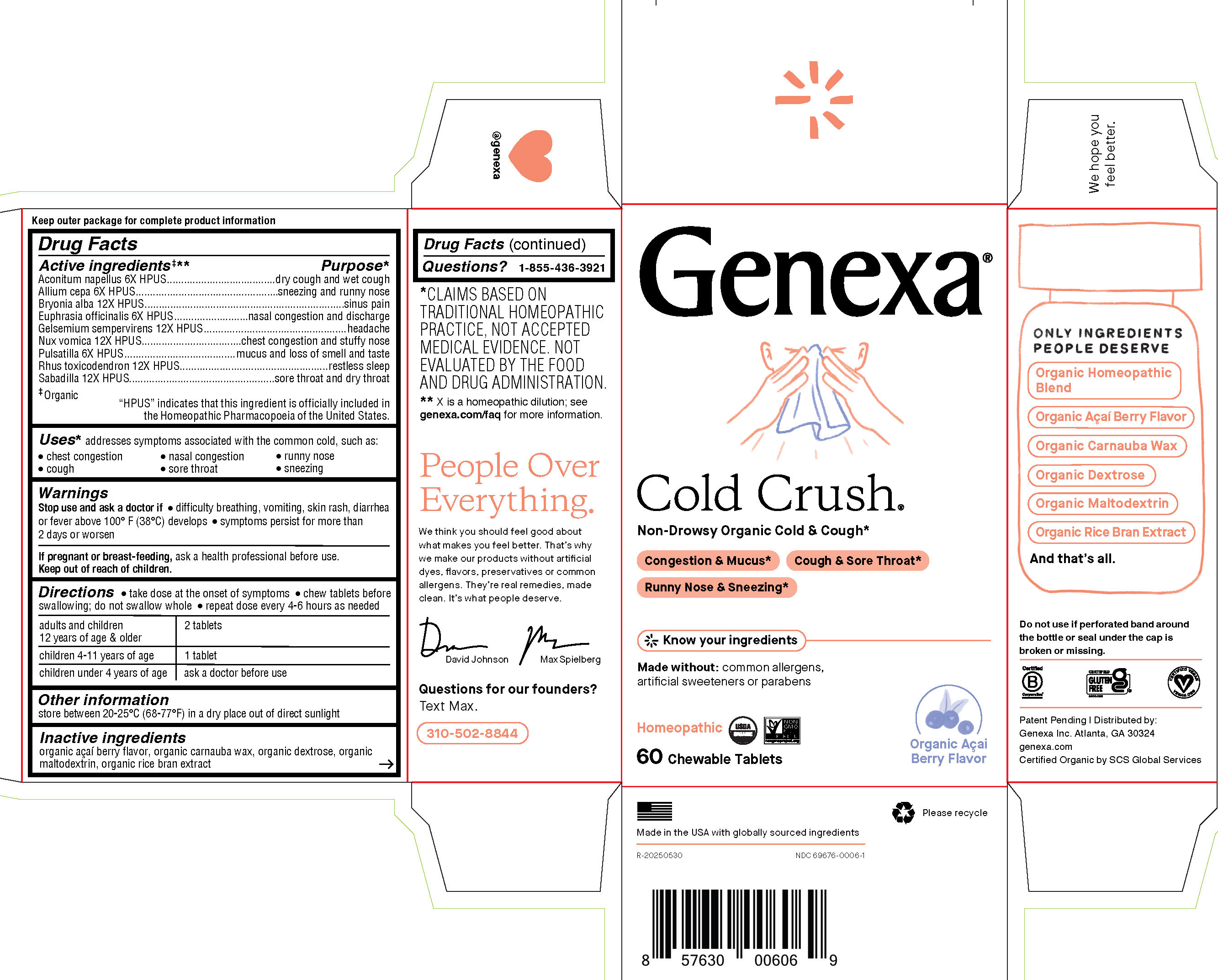 DRUG LABEL: Cold Crush Adult
NDC: 69676-0006 | Form: TABLET, CHEWABLE
Manufacturer: Genexa Inc.
Category: homeopathic | Type: HUMAN OTC DRUG LABEL
Date: 20251215

ACTIVE INGREDIENTS: PULSATILLA PRATENSIS 6 [hp_X]/1 1; GELSEMIUM SEMPERVIRENS ROOT 12 [hp_X]/1 1; ONION 6 [hp_X]/1 1; ACONITUM NAPELLUS 6 [hp_X]/1 1; BRYONIA ALBA ROOT 12 [hp_X]/1 1; EUPHRASIA STRICTA 6 [hp_X]/1 1; TOXICODENDRON PUBESCENS SHOOT 12 [hp_X]/1 1; STRYCHNOS NUX-VOMICA SEED 12 [hp_X]/1 1; SCHOENOCAULON OFFICINALE SEED 12 [hp_X]/1 1
INACTIVE INGREDIENTS: ACAI; RICE BRAN; DEXTROSE; MALTODEXTRIN; CARNAUBA WAX

COLD CRUSH, ADULT

Drug Facts

Active ingredients‡**

Aconitum napellus 6X HPUS

Allium cepa 6X HPUS

Bryonia alba 12X HPUS

Euphrasia officinalis 6X HPUS

Gelsemium sempervirens 12X HPUS

Nux vomica 12X HPUS

Pulsatilla 6X HPUS

Rhus toxicodendron 12X HPUS

Sabadilla 12X HPUS

‡ Organic

"HPUS" indicates that this ingredient is officially included in the Homeopathic Pharmacopoeia of the United States.

Purpose*

dry cough and wet cough

sneezing and runny nose

sinus pain

nasal congestion and discharge

headache

chest congestion and stuffy nose

mucus and loss of smell and taste

restless sleep

sore throat and dry throat

Uses*

addresses symptoms associated with the common cold, such as:

- chest congestion
- nasal congestion
- runny nose
- cough
- sore throat
- sneezing

Warnings

Stop use and ask a doctor if

- difficulty breathing, vomiting, skin rash, diarrhea or fever above 100°F (38°C) develops
- symptoms persist for more than 2 days or worsen

PREGNANCY OR BREAST FEEDING

If pregnant or breast-feeding, ask a health professional before use.

Keep out of reach of children.

Directions

- take dose at the onset of symptoms
- chew tablets before swallowing; do not swallow whole
- repeat dose every 4-6 hours as needed

adults and children 12 years of age; & older | 2 tablets
children 4-11 years of age | 1 tablet
children under 4 years of age | ask a doctor before use

Other information

store between 20-25°C (68-77°F) in a dry place out of direct sunlight

Inactive ingredients

organic açaÍ berry flavor, organic carnauba wax, organic dextrose, organic maltodextrin, organic rice bran extract

Questions?

1-855-436-3921

* CLAIMS BASED ON TRADITIONAL HOMEOPATHIC PRACTICE, NOT ACCEPTED MEDICAL EVIDENCE. NOT EVALUATED BY THE FOOD AND DRUG ADMINISTRATION.
** X is a homeopathic dilution; see genexa.com/faq for more information.

Do not use if perforated band around the bottle or seal under the cap is broken or missing.
Patent Pending | Distributed by:

Genexa Inc. Atlanta, GA 30324

genexa.com
Certified Organic by SCS Global Services

Made in the USA with globally sourced ingredients

NDC 69676-0006-1

PACKAGE LABEL

Genexa®

Cold Crush®

Non-Drowsy Organic Cold & Cough*

Congestion & Mucus*

Cough & Sore Throat*

Runny Nose & Sneezing*

Know your ingredients

Made without: common allergens, artificial sweeteners or parabens

Homeopathic

60 Chewable Tablets

Organic AçaÍ Berry Flavor